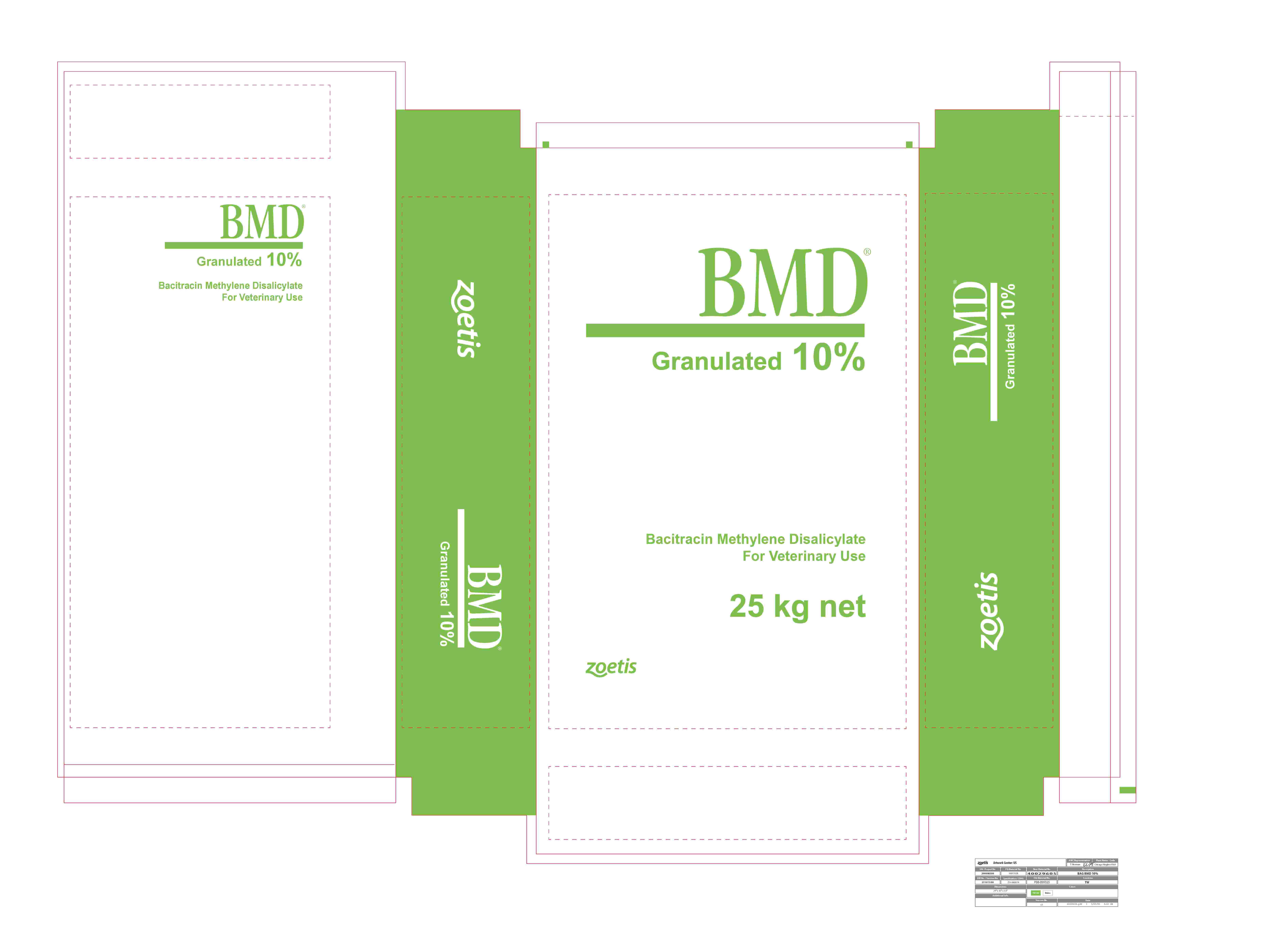 DRUG LABEL: BMD 10%
NDC: 66104-6409 | Form: GRANULE
Manufacturer: Phibro Animal Health
Category: animal | Type: OTC ANIMAL DRUG LABEL
Date: 20250219

ACTIVE INGREDIENTS: BACITRACIN METHYLENEDISALICYLATE 50 g/0.45 kg

BMD 10%

DESCRIPTION

BMD 10%

Species Dose Indications for Use

Broiler and replacement chickens: 4 - 50 For increased rate of weight gain and improved feed efficiency.

50 As an aid in prevention of necrotic enteritis caused or complicated

by Clostridium spp. or other organisms susceptible to bacitracin methylene disalicylate.

100-200 As an aid in control of necrotic enteritis caused or complicated by
Clostridium spp. or other organisms susceptible to bacitracin
methylene disalicylate.

CAUTION: To control a necrotic enteritis outbreak, start medication
at the first clinical signs of disease. The dosage range permitted
provides for different levels based on severity of the infection.
Consult a poultry diagnostic laboratory or pathologist to determine
the diagnosis and advice regarding the optimal level of drug.
Administer continuously for 5 - 7 days or as long as clinical signs
persist, and then reduce medication to prevention level (50 g/ton).

Laying Hens: 10 - 25 For increased egg production and improved feed efficiency during
the first seven months of production

Growing turkeys: 4 - 50 For increased rate of weight gain and improved feed efficiency.

200 As an aid in control of transmissible enteritis in growing turkeys
complicated by organisms susceptible to bacitracin methylene
disalicylate.

Pheasants: 4 - 50 For increased rate of weight gain and improved feed efficiency.

Quail: 5 - 20 For increased rate of weight gain and improved feed efficiency in
quail not over 5 weeks of age.

200 For prevention of ulcerative enteritis in growing quail due to
Clostridium colinum susceptible to bacitracin methylene disalicylate.
Feed continuously as the sole ration.

Growing/Finishing Swine: 10 - 30 For increased rate of weight gain and improved feed efficiency.

250 For control of swine dysentery (bloody scours) associated with
Brachyspira hyodysenteriae in pigs up to 250 lbs body weight. Feed
250 grams per ton of complete feed on premises with a history of
swine dysentery, but where signs of the disease have not yet
occurred or following an approved treatment of the disease
condition.

The 250 g/ton level will provide 5 to 7 mg/lb in swine weighing 40 to
250 lbs.

CAUTION: Diagnosis should be confirmed by a veterinarian when
results are not satisfactory. Feed containing an approved level of
bacitracin methylene disalicylate should be the sole ration.

Pregnant Sows: 250 For control of clostridial enteritis caused by C. perfringens in
suckling piglets when fed to sows from 14 days before through 21
days after farrowing on premises with a history of clostridial scours.

mg/head/day CAUTION: Diagnosis should be confirmed by a veterinarian when
results are not satisfactory. Feed containing an approved level of
bacitracin methylene disalicylate should be the sole ration.

Feedlot beef cattle: 70 For reduction in the number of liver condemnations due to
(continuously) abscesses in feedlot beef cattle.

250 For reduction in the number of liver condemnations due to
(continuously) abscesses in feedlot beef cattle.

Note: Where minimum levels are shown, increase the antibiotic concentration within approved range when
necessary to fit the feeding program, and to insure adequate levels of antibiotic in the complete ration.

BMD 10 Label